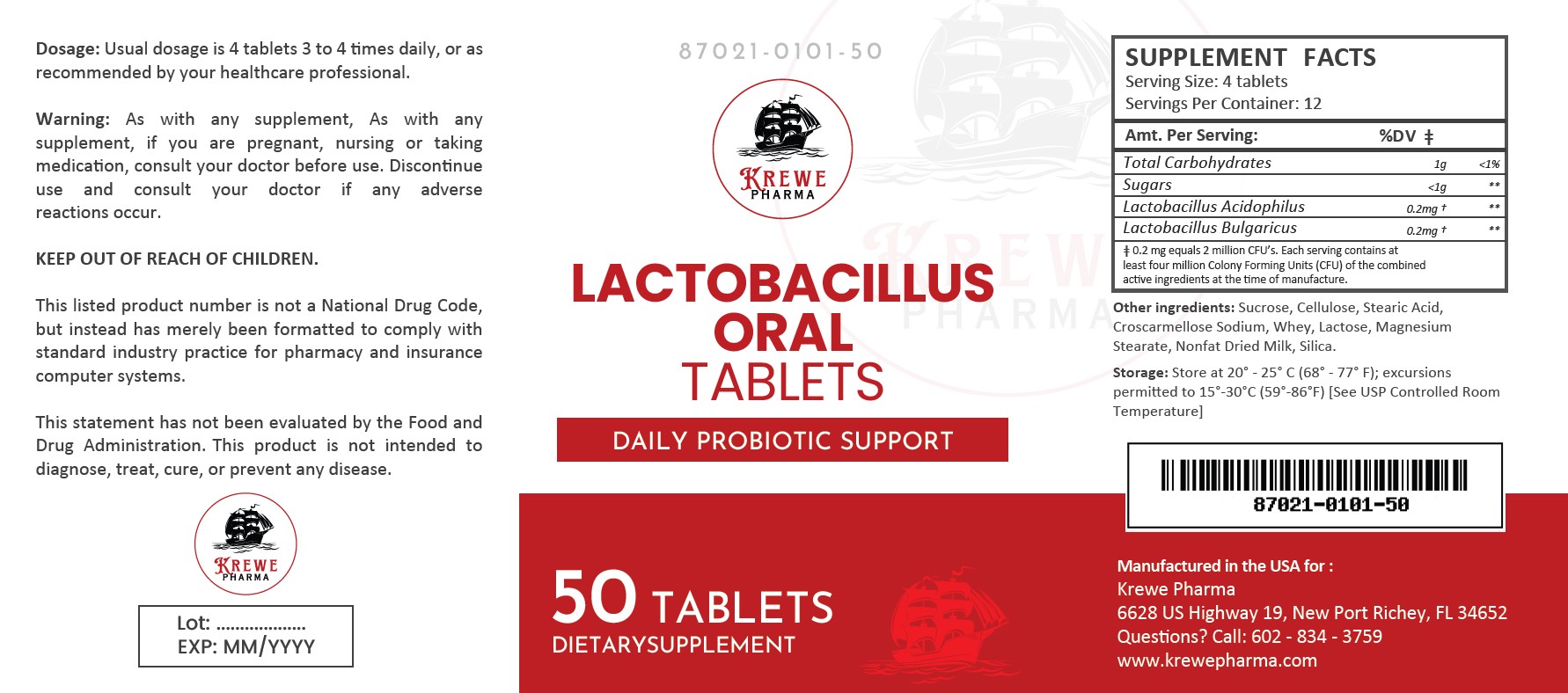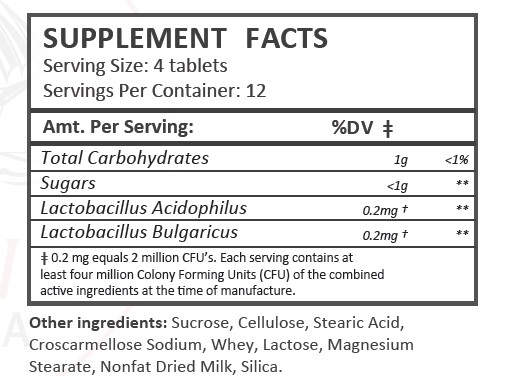 DRUG LABEL: Lactobacillus
NDC: 87021-101 | Form: TABLET
Manufacturer: Krewe Pharma, LLC
Category: other | Type: DIETARY SUPPLEMENT
Date: 20251028

ACTIVE INGREDIENTS: LACTOBACILLUS ACIDOPHILUS 0.2 mg/1 1; LACTOBACILLUS DELBRUECKII BULGARICUS 0.2 mg/1 1

Lactobacillus Tablets

Description:

FloraMax is supplied as white, round tablets dispensed in plastic bottles of 50 ct.

87021-0101-50

Reserved for Professional Recommendation

This listed product is not a National Drug Code, but instead has merely been formatted to comply with standard industry practice for pharmacy and insurance computer systems.

These statements have not been evaluated by the Food and Drug Administration. This product is not intended to diagnose, treat, cure or prevent any disease.

All prescriptions using this product shall be pursuant to state statutes as applicable. This is not an Orange Book product. This product may be administered only under a physician’s supervision. There are no implied or explicit claims on therapeutic equivalence.

Manufactured for:

Krewe Pharma

New Port Richey, FL 34652

Warnings:

This product is contraindicated in patients with a known hypersensitivity to any of the ingredients.

As with any supplement, if you are pregnant, nursing, taking medication, or have a medical condition, ask a health professional before taking this product.

These statements have not been evaluated by the Food and Drug Administration. This product is not intended to diagnose, treat, cure, or prevent any disease.

Dosage and Administration:

Usual dosage is 4 tablets 3 to 4 times daily, or as recommended by your healthcare professional.

Precautions:

CONTRAINDICATIONS
This product is contraindicated in patients with known hypersensitivity to any of the ingredients.

PRECAUTIONS
This product is contraindicated in patients with a known hypersensitivity to any of the ingredients.

ADVERSE REACTIONS
Allergic sensitizations have been reported following oral administration of folic acid. Consult your physician immediately if adverse side effects occur.

KEEP OUT OF THE REACH OF CHILDREN.

Storage:

Store at 20° - 25° C (68° - 77° F); excursions permitted to 15°-30°C (59°-86°F)[See USP Controlled Room Tempature].